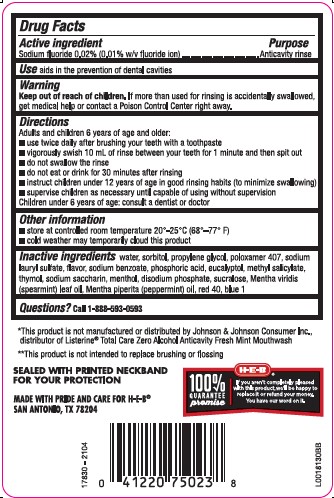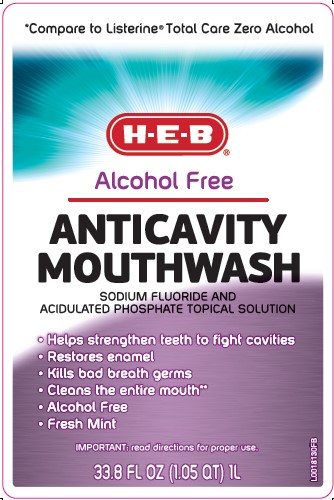 DRUG LABEL: Anticavity
NDC: 37808-119 | Form: RINSE
Manufacturer: H E B
Category: otc | Type: HUMAN OTC DRUG LABEL
Date: 20260224

ACTIVE INGREDIENTS: SODIUM FLUORIDE 0.1 mg/1 mL
INACTIVE INGREDIENTS: WATER; SORBITOL; PROPYLENE GLYCOL; POLOXAMER 407; SODIUM LAURYL SULFATE; SODIUM BENZOATE; PHOSPHORIC ACID; EUCALYPTOL; METHYL SALICYLATE; THYMOL; SACCHARIN SODIUM; MENTHOL; SODIUM PHOSPHATE, DIBASIC, ANHYDROUS; SUCRALOSE; SPEARMINT OIL; PEPPERMINT OIL; FD&C RED NO. 40; FD&C BLUE NO. 1

HEB 971.001/971AB
Burn-Free Fluoride Anti-Cavity Mouthwash

active ingredients

Sodium fluoride 0.0% (0.01% w/v fluoride ion)

Purpose

Anticavity rinse

Use

aids in the prevention of dental cavities

Warning

For this product

Keep out of Reach of Children.

If more than used for rinsing is accidentally swallowed, get medical help or contact a Poison Control Center right away.

Directions

Adults and children 6 years of age and older:

- use twice daily after brushing your teeth with a toothpaste
- vigorously swish 10 mL (2 teaspoonfuls) of rinse between your teeth for 1 miute and then spit out.
- do not swallow the rinse
- do not eat or drink for 30 minutes after rinsing
- instruct children under 12 years of age in good rinsing habits (to minimize swallowing)
- supervise children as necessary until capable of using without supervision
- children under 6 years of age: consult a dentist or doctor

Other information

- store at room temperature 20⁰ - 25⁰ C (68⁰ - 77⁰ F)
- cold weather may temporarily cloud this product

Inactive ingredients

water, sorbitol, propylene glycol, poloxamer 407, sodium lauryl sulfate, flavor, sodium benzoate, phosphoric acid, eucalyptol, methyl salicylate, thymol, sodium saccharin, menthol, disodium phosphate, sucralose, Mentha viridis (spearmint) leaf oil, Mentha piperita (peppermint) oil, red 40, blue 1

Questions?

Call 1-888-593-0593

Disclaimer

*This product is not manufactured or distributed by Johnson & Johnson Consumer Inc., distributor of Listerine®Total Care Zero Alcohol Anticavity Fresh Mint Mouthwash.

**This product is not intended to replace brushing or flossing.

Tamper Evident Statement

SEALED WITH PRINTED NECKBAND FOR YOUR PROTECTION

Adverse reactions section

MADE WITH PRIDE AND CARE FOR H-E-B

SAN ANTONIO, TX 78204

100% GUARANTEE promise

If you aren't completely pleased with this product, we'll be happy to replace it or refund your money.

You have our word on it.

principal display panel

*Compare to Listerine®Total Care Zero Alcohol

H-E-B®

Alcohol Free

ANTICAVITY

MOUTHWASH

SODIUM FLUORIDE AND ACIDULATED PHOSPHATE TOPCAL SOLUTION

- Helps strengthen teeth to fight cavities
- Restored enamel
- Kills bad breath germs
- Cleans the entire mouth**
- Alcohol Free
- Fresh Mint

IMPORTANT: read directions for proper use

33.8 FL OZ (1.05 QT) 1 L